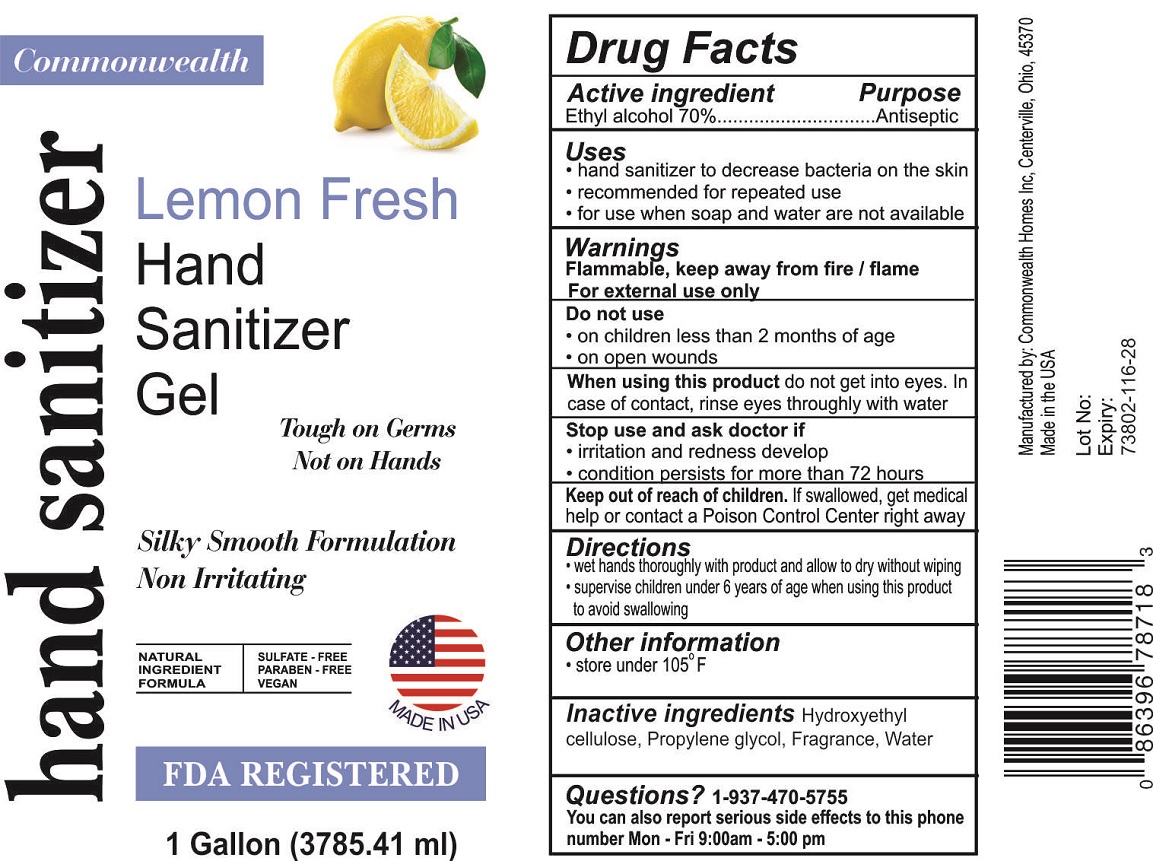 DRUG LABEL: Commonwealth Lemon Fresh Hand Sanitizer Gel
NDC: 73802-116 | Form: GEL
Manufacturer: Commonwealth Homes, Inc.
Category: otc | Type: HUMAN OTC DRUG LABEL
Date: 20201013

ACTIVE INGREDIENTS: ALCOHOL 70 mL/100 mL
INACTIVE INGREDIENTS: HYDROXYETHYL CELLULOSE, UNSPECIFIED; PROPYLENE GLYCOL; WATER

Commonwealth Lemon Fresh Hand Sanitizer Gel

Active ingredient

Ethyl alcohol 70%

Purpose

Antiseptic

Uses

• hand sanitizer to decrease bacteria on the skin

• recommended for repeated use

• for use when soap and water are not available

Warnings

Flammable, keep away from fire / flame

For external use only

Do not use

• on children less than 2 months of age

• on open wounds

When using this product do not get into eyes. In case of contact, rinse eyes thoroughly with water

Stop use and ask doctor if

• irritation and redness develop

• condition persists for more than 72 hours

Keep out of reach of children. If swallowed, get medical help or contact a Poison Control Center right away

Directions

• wet hands thoroughly with product and allow to dry without wiping

• supervise children under 6 years of age when using this product to avoid swallowing

Other information

• store under 105° F

INACTIVE INGREDIENT

Inactive ingredients Hydroxyethyl cellulose, Propylene glycol, Fragrance, Water

Questions? 1-937-470-5755

You can also report serious side effects to this phone number Mon - Fri 9:00am - 5:00 pm

Lemon Fresh

Tough on Germs

Not on Hands

Silky Smooth Formulation

Non Irritating

NATURAL INGREDIENT FORMULA

SULFATE - FREE

PARABEN - FREE

VEGAN

MADE IN USA

FDA REGISTERED

Manufactured by: Commonwealth Homes Inc, Centerville, Ohio, 45370